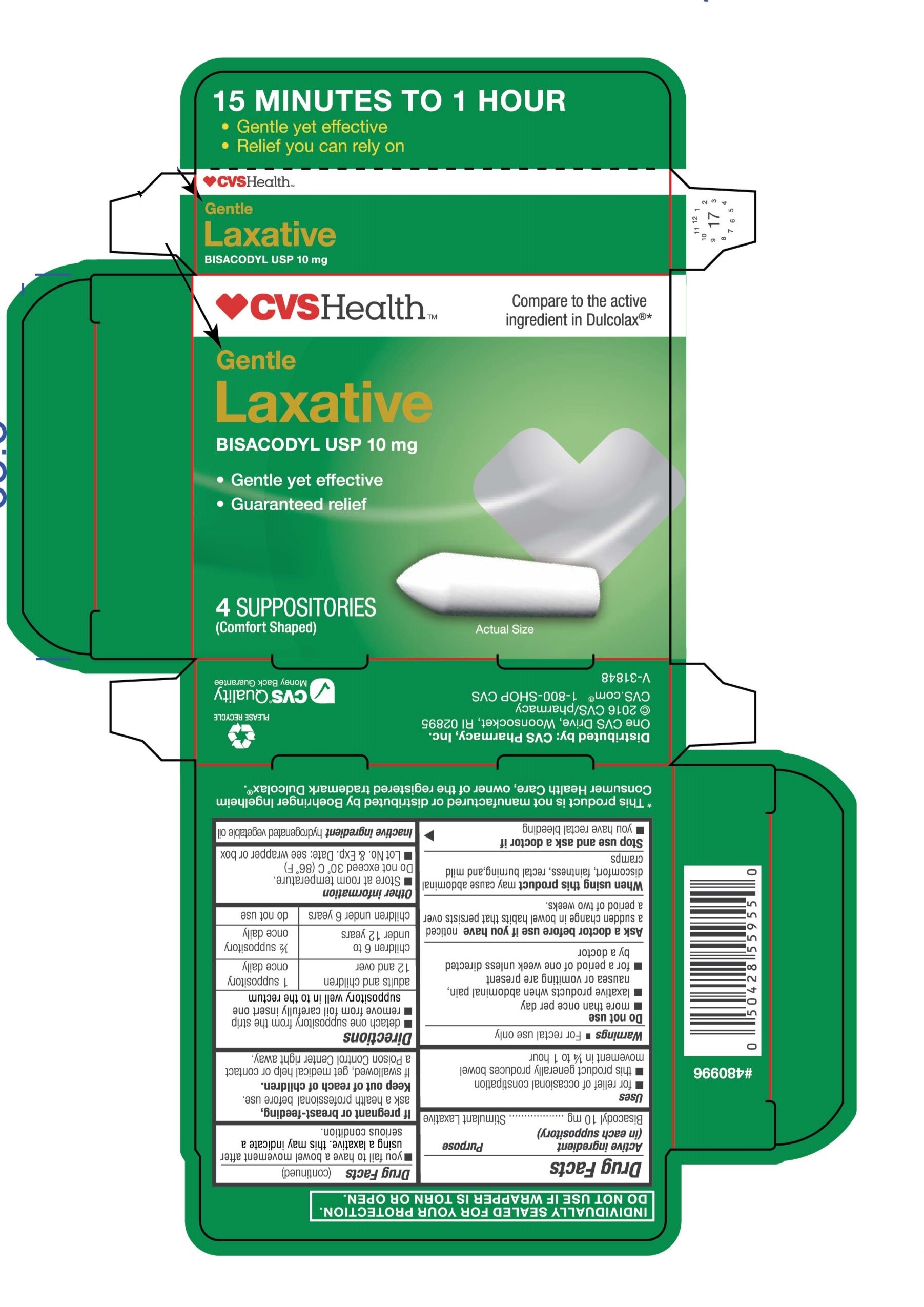 DRUG LABEL: CVS Gentle Laxative
NDC: 59779-107 | Form: SUPPOSITORY
Manufacturer: CVS Pharmacy
Category: otc | Type: HUMAN OTC DRUG LABEL
Date: 20260114

ACTIVE INGREDIENTS: BISACODYL 10 mg/1 1
INACTIVE INGREDIENTS: PALM KERNEL OIL

CVS Pharmacy®Gentle Laxatives 4 ct

Active Ingredient (in each Suppository)

Purpose

Bisacodyl USP, 10 mg.................................Stimulant Laxative

Uses

Uses - For relief of occasional constipation and irregularity

-This product generally produces bowel movement in 15 minutes to 1 hour

Warnings

For rectal use only.

Do not use - more than once per day - for a period of longer than one week unless directed by a doctor - laxative products when abdominal pain, nausea, or vomiting are present unless directed by a doctor

Ask a doctor before use if you have - noticed a sudden change in bowel habits that persists over a period of two weeks

When using this product - May cause abdominal discomfort, faintness, rectal burning, and mild cramps

Stop use and ask a doctor if you have rectal bleeding or fail to have bowel movement after using a laxative. This may indicate a serious condition

If pregnant or breast-feeding, ask a health professional before use.

Keep out of reach of children. If swallowed, get medical help or contact a Poison Control Center right away.

Directions

Adults and children 12 years of age and older Children 6 to under 12 years Children under 6

One suppository once daily 1/2 suppository once daily Ask doctor.

-Detach one suppository from the strip and remove from foil - Carefully insert one suppository well into the rectum

-Do not use more than once per day

Other information

Other information - Store at room temperature: 15o - 30oC (59o - 86oF). Do not exceed 30oC (86oF) - Individually sealed for your protection. Do not use if foil is torn or open

Inactive ingredient

Inactive ingredient Hydrogenated vegetable oil

Purpose

Stimulant Laxative